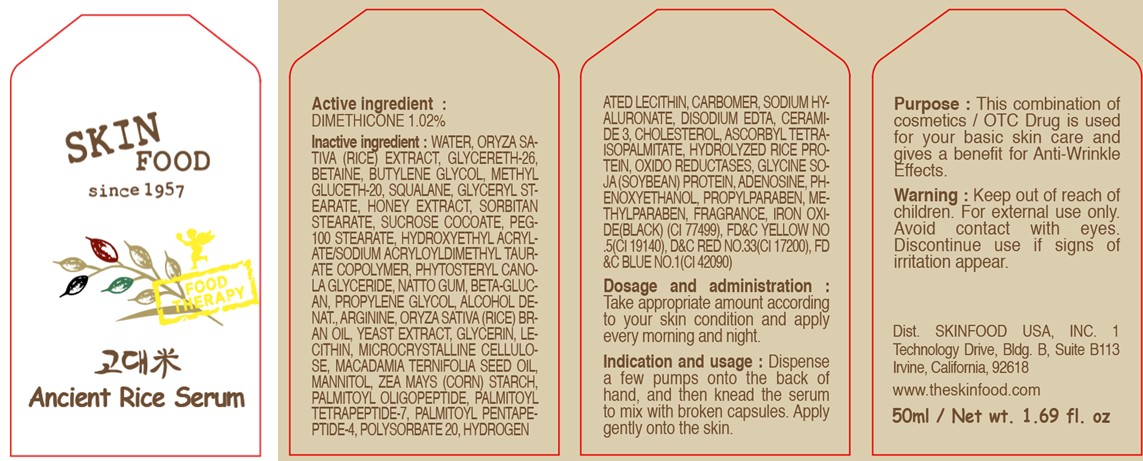 DRUG LABEL: ANCIENT RICE SERUM
NDC: 76214-011 | Form: CREAM
Manufacturer: SKINFOOD CO., LTD.
Category: otc | Type: HUMAN OTC DRUG LABEL
Date: 20110801

ACTIVE INGREDIENTS: DIMETHICONE 0.51 mL/50 mL
INACTIVE INGREDIENTS: WATER; RICE; GLYCERETH-26; BETAINE; BUTYLENE GLYCOL; METHYL GLUCETH-20; SQUALANE; GLYCERYL MONOSTEARATE; HONEY; SORBITAN MONOSTEARATE; SUCROSE COCOATE; PEG-100 STEARATE; PROPYLENE GLYCOL; METHYLPARABEN; ARGININE; RICE BRAN OIL; YEAST; GLYCERIN; LECITHIN, SOYBEAN; MACADAMIA OIL; MANNITOL; STARCH, CORN; PALMITOYL OLIGOPEPTIDE; PALMITOYL TETRAPEPTIDE-7; PALMITOYL PENTAPEPTIDE-4; POLYSORBATE 20; HYDROGENATED SOYBEAN LECITHIN; PHENOXYETHANOL; PROPYLPARABEN; ADENOSINE; HYALURONATE SODIUM; EDETATE DISODIUM; CERAMIDE 3; CHOLESTEROL; SOYBEAN

Drug Facts

Active ingredient: DIMETHICONE 1.02%

Inactive ingredients:

WATER, ORYZA SATIVA (RICE) EXTRACT, GLYCERETH-26, BETAINE, BUTYLENE GLYCOL, METHYL GLUCETH-20, SQUALANE, GLYCERYL STEARATE, HONEY EXTRACT, SORBITAN STEARATE, SUCROSE COCOATE, PEG-100 STEARATE, HYDROXYETHYL ACRYLATE/SODIUM ACRYLOYLDIMETHYL TAURATE COPOLYMER, PHYTOSTERYL CANOLA GLYCERIDE, NATTO GUM, BETA-GLUCAN, PROPYLENE GLYCOL, ALCOHOL DENAT., ARGININE, ORYZA SATIVA (RICE) EXTRACT, YEAST EXTRACT, GLYCERIN, LECITHIN, MICROCRYSTALLINE CELLULOSE, MACADAMIA TERNIFOLIA SEED OIL, MANNITOL, ZEA MAYS (CORN) STARCH, PALMITOYL OLIGOPEPTIDE, PALMITOYL TETRAPEPTIDE-7, PALMITOYL PENTAPEPTIDE-4, POLYSORBATE 20, HYDROGENATED LECITHIN, CARBOMER, SODIUM HYALURONATE, DISODIUM EDTA, CERAMIDE 3, CHOLESTEROL, ASCORBYL TETRAISOPALMITATE, HYDROLYZED RICE PROTEIN, OXIDO REDUCTASES, GLYCINE SOJA (SOYBEAN) PROTEIN, ADENOSINE, PHENOXYETHANOL, PROPYLPARABEN, METHYLPARABEN, FRAGRANCE

Purpose:

This combination of cosmetics is used for your basic skin care and gives a benefit for Anti-Wrinkle Effects.

Warnings:

For external use only. Avoid contact with eyes. Discontinue use if signs of irritation appear.

Keep out of reach of children:

Keep out of reach of children.

Indication and usage:

Dispense a few pumps onto the back of hand, and then knead the serum to mix with broken capsules. Apply gently onto the skin.

Dosage and administration:

Take appropriate amount according to your skin condition and apply every morning and night.